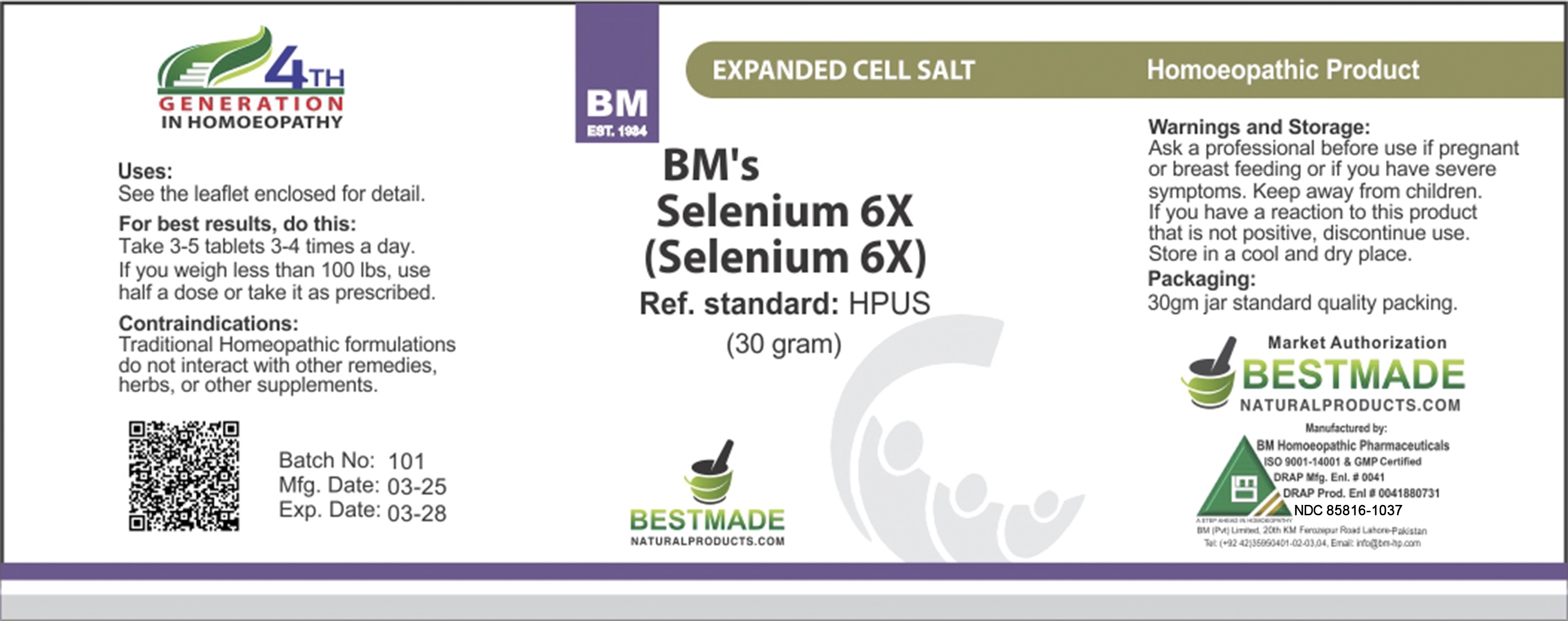 DRUG LABEL: BM Selenium (Selenium)
NDC: 85816-1037 | Form: TABLET
Manufacturer: BM Private Limited
Category: homeopathic | Type: HUMAN OTC DRUG LABEL
Date: 20251202

ACTIVE INGREDIENTS: SELENIUM 6 [hp_X]/60 mg
INACTIVE INGREDIENTS: MAGNESIUM STEARATE 1.2 mg/60 mg; LACTOSE 58.75 mg/60 mg

BM Selenium (Selenium)

Directions:
Adult: Four tablets three times a day.
Ages below 12: half of the same or as prescribed by a homeopathic physician.

Inactive ingredients: Lactose; MAGNESIUM STEARATE

ACTIVE INGREDIENT

Selenium

Uses
See the leaflet enclosed for detail.

Uses
See the leaflet enclosed for detail.

CONTRAINDICATIONS

Contra-indications:
Traditional biochemic remedy do not interact with other remedies, herbs, or other supplements.

Warnings and Storage:
Ask a professional before use if pregnant or breastfeeding or if you have severe symptoms. Keep away from children. If you have a reaction to this product that is not positive, discontinue use. Store in a cool and dry place.

KEEP OUT OF REACH OF CHILDREN

Warnings and Storage:
Ask a professional before use if pregnant or breastfeeding or if you have severe symptoms. Keep away from children. If you have a reaction to this product that is not positive, discontinue use. Store in a cool and dry place.

Entire package